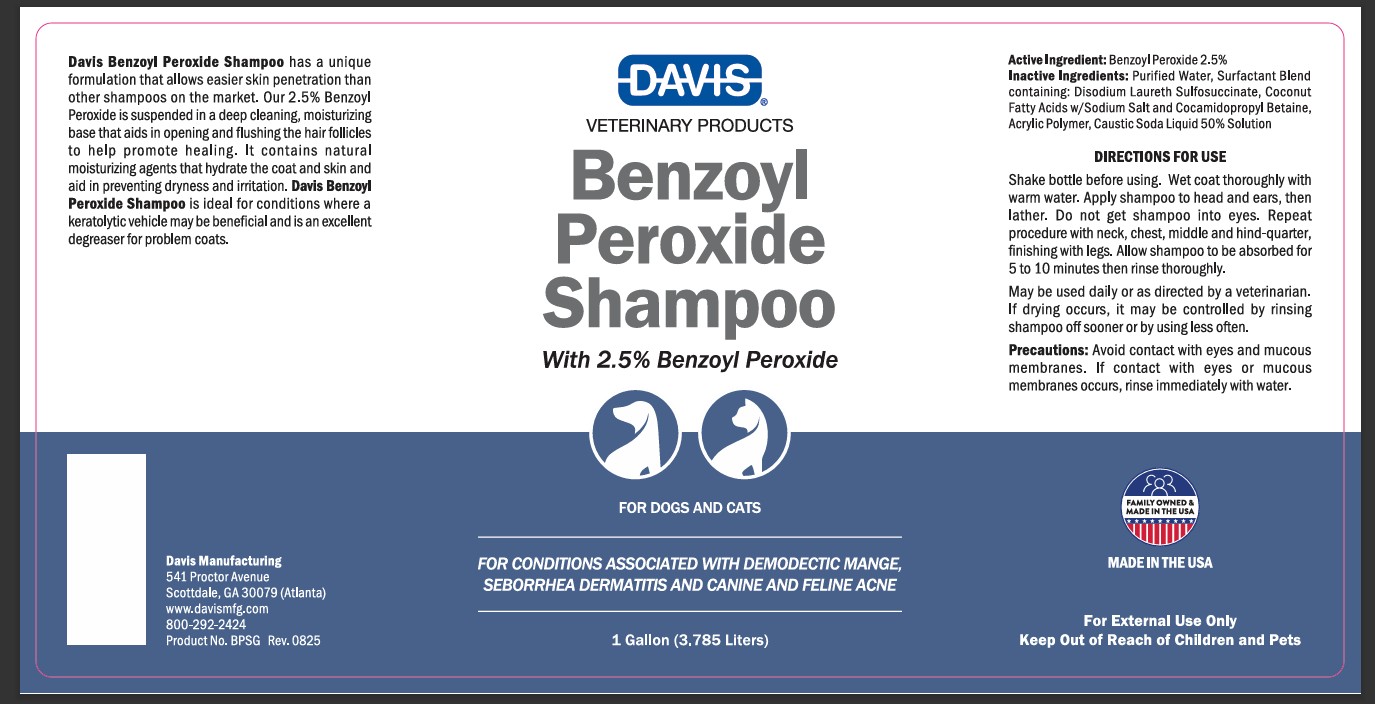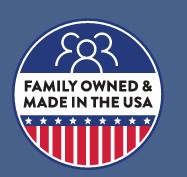 DRUG LABEL: Davis Benzoyl Peroxide
NDC: 62570-011 | Form: SHAMPOO
Manufacturer: Davis Manufacturing and Packaging Inc
Category: animal | Type: OTC ANIMAL DRUG LABEL
Date: 20191104

ACTIVE INGREDIENTS: BENZOYL PEROXIDE 2.5 g/100 g
INACTIVE INGREDIENTS: water; METHACRYLIC ACID - ETHYL ACRYLATE COPOLYMER (1:1) TYPE A; PROPYLENE GLYCOL; SODIUM HYDROXIDE

Benzoyl Peroxide Shampoo

Active Ingredient: Benzoyl Peroxide 2.5%

INACTIVE INGREDIENT

INACTIVE INGREDIENTS: Purified Water, Surfactant Blend containing: Disodium Laureth Sulfosuccinate, Coconut Fatty Acids w/Sodium Salts and Cocamidopropyl Betaine, Acrylic Polymer, Caustic Soda Liquid 50% Solution

INSTRUCTIONS FOR USE

Directions for Use: Shake bottle before using. Wet coat thoroughly with warm water. Apply shampoo to head and ears, then lather. Do not get shampoo into eyes. Repeat procedure with neck, chest, middle and hind-quarter, finishing with legs. Allow shampoo to be absorbed for 5 to 10 minutes then rinse thoroughly.

May be used daily or as directed by a veterinarian. If drying occurs, it may be controlled by rinsing the shampoo off sooner or by using less often.

GENERAL PRECAUTIONS

Precautions: Avoid contact with eyes and mucous membranes. If contact with eyes occurs, rinse immediately with water.

INDICATIONS AND USAGE

Benzoyl Peroxide Shampoo has a unique formulation that allows easier skin penetration than other shampoos on the market. Our 2.5% Benzoyl Peroxide is suspended in a deep cleaning, moisturizing base that aids in opening and flushing the hair follicles to help promote healing. It contains natural moisturizing agents that hydrate the coat and skin and aid in preventing dryness and irritation. Davis Benzoyl Peroxide Shampoo is ideal for conditions where a keratolytic vehicle may be beneficial and is an excellent degreaser for problem coats.

MADE IN THE USA

PACKAGE LABEL

Davis Veterinary Products

Benzoyl Peroxide Shampoo

with 2.5% Benzoyl Peroxide

FOR DOGS AND CATS

For Conditions associated with demodectic mange, seborrhea dermatitis and canine and feline acne

12 Fl. Oz. (355 ml)

PACKAGE LABEL

Davis Veterinary Products

Benzoyl Peroxide Shampoo

with 2.5% Benzoyl Peroxide

FOR DOGS AND CATS

For Conditions associated with demodectic mange, seborrhea dermititis and canine and feline acne

1 Gallon (3.785 Liters)